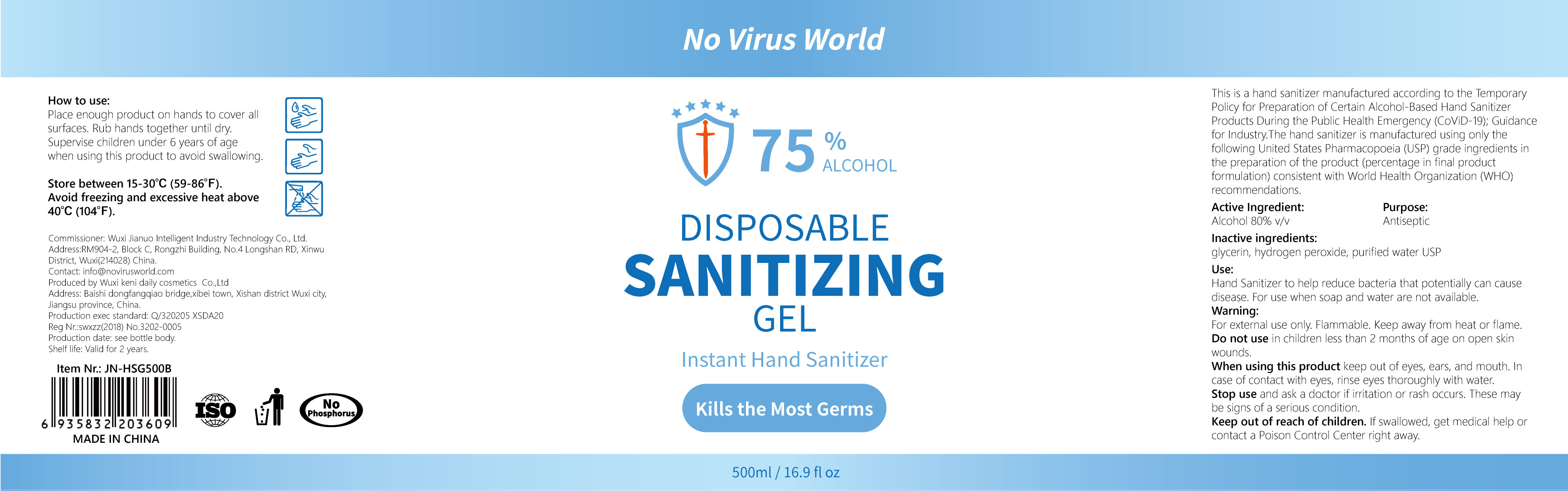 DRUG LABEL: Disposable Sanitizing Gel
NDC: 75211-001 | Form: GEL
Manufacturer: Wuxi Jianuo Intelligent Industrial Technology Co., Ltd.
Category: otc | Type: HUMAN OTC DRUG LABEL
Date: 20200426

ACTIVE INGREDIENTS: ALCOHOL 80 mL/100 mL
INACTIVE INGREDIENTS: HYDROGEN PEROXIDE; GLYCERIN

Disposable Sanitizing Gel

Active Ingredient

Alcohol 80%v/v

Purpose

Antiseptic

Use

Hand Sanitizer to help reduce bacteria that potentially can cause disease.For use when soap and water are not available.

Warning

For external use only.Flammable.Keep away from heat or flame.

Do not use

in children less than 2 months of age on open skin wounds.

When using this product

keep out of eyes, ears, and mouth.In case of contact with eyes, rinse eyes thoroughly with water.

Stop use

Stop use and ask a doctor if irritation or rash occurs.These may be signs of a serious condition.

Keep out of reach of children

If swallowed, get medical help or contact a Poison Control Center right away.

Other information

Store between 15-30℃(59-86°F) .

Avoid freezing and excessive heat above 40℃(104°F).

Inactive ingredients

glycerin, hydrogen peroxide,purified water USP